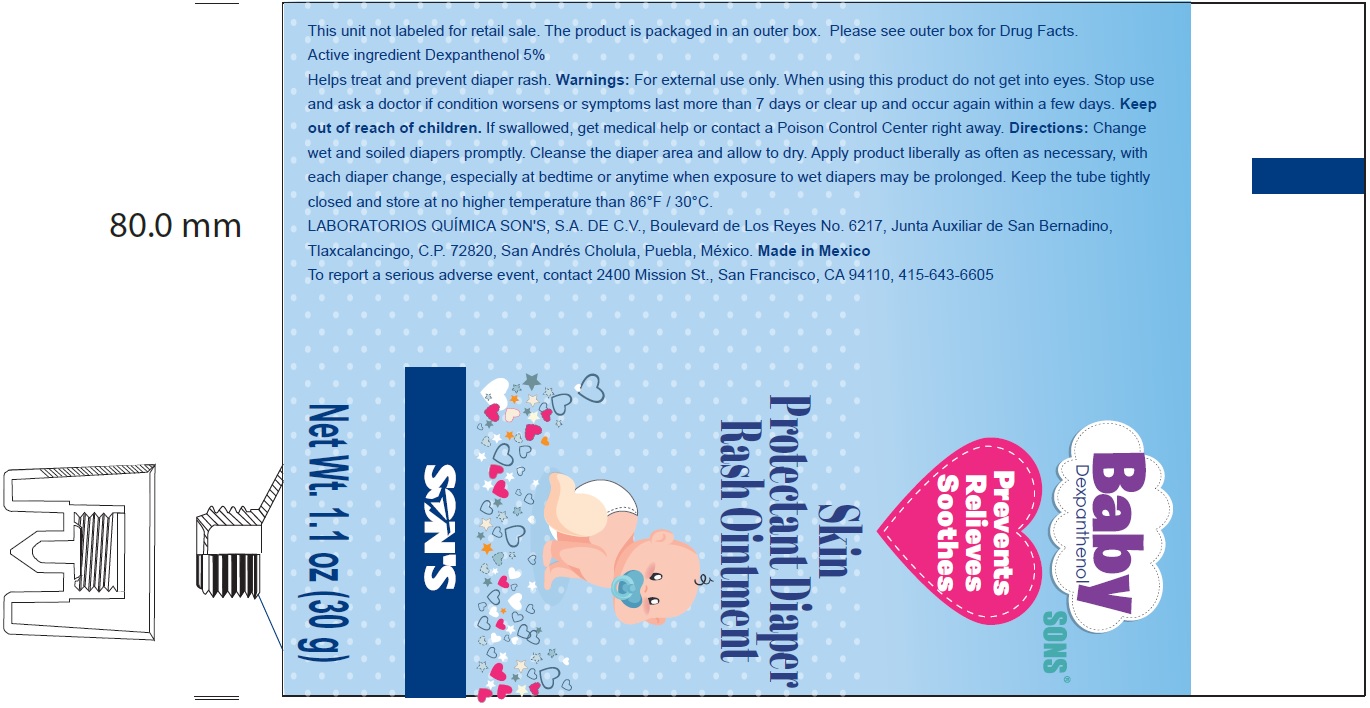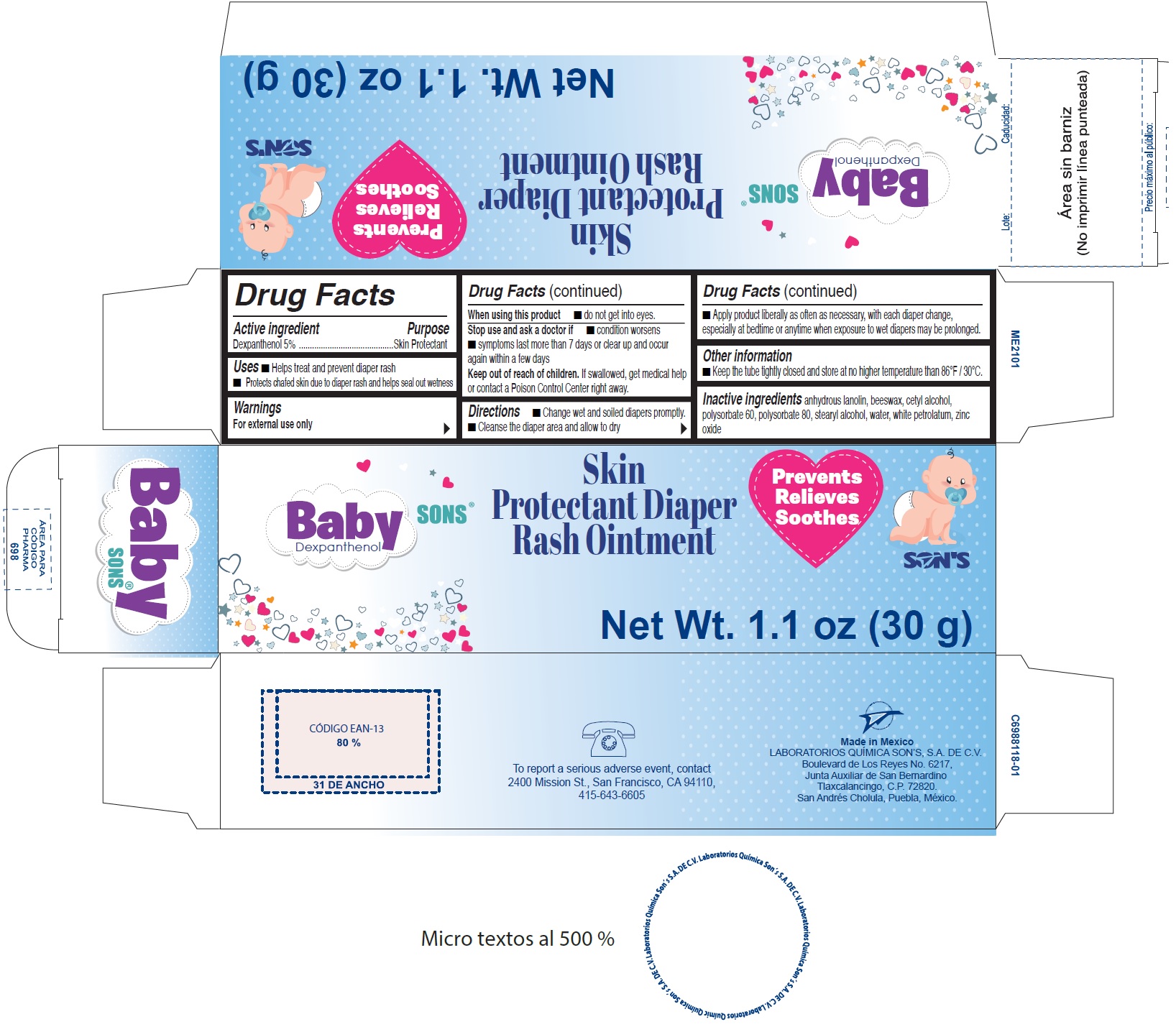 DRUG LABEL: BABYSONS
NDC: 73519-001 | Form: OINTMENT
Manufacturer: Laboratorios Quimica Son's, S.A. de C.V
Category: otc | Type: HUMAN OTC DRUG LABEL
Date: 20241031

ACTIVE INGREDIENTS: DEXPANTHENOL 50 mg/1 g
INACTIVE INGREDIENTS: LANOLIN; YELLOW WAX; CETYL ALCOHOL; POLYSORBATE 60; POLYSORBATE 80; STEARYL ALCOHOL; WATER; PETROLATUM; ZINC OXIDE

BABYSONS

Active ingredient

Dexpanthenol 5%

Purpose

Skin Protectant

Uses

- Helps treat and prevent diaper rash
- Protects chafed skin due to diaper rash and helps seal out wetness

Warnings

For external use only

When using this product

- do not get into eyes.

Stop use and ask a doctor if

- condition worsens
- symptoms last more than 7 days or clear up and occur again within a few days

Keep out of reach of children.

If swallowed, get medical help or contact a Poison Control Center right away.

Directions

- Change wet and soiled diapers promptly.
- Cleanse the diaper area and allow to dry
- Apply product liberally as often as necessary, with each diaper change, especially at bedtime or anytime when exposure to wet diapers may be prolonged.

Other information

Keep the tube tightly closed and store at no higher temperature than 86°F / 30°C.

Inactive ingredients

anhydrous lanolin, beeswax, cetyl alcohol, polysorbate 60, polysorbate 80, stearyl alcohol, water, white petrolatum, zinc oxide